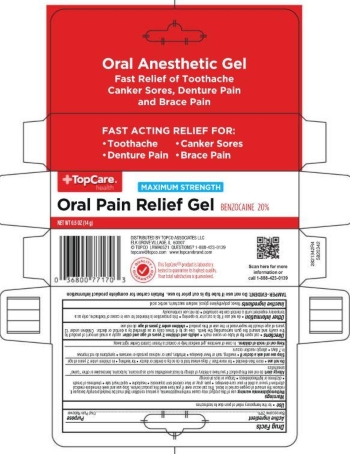 DRUG LABEL: TopCare Oral Pain Relief
NDC: 36800-512 | Form: GEL
Manufacturer: Topco Associates LLC
Category: otc | Type: HUMAN OTC DRUG LABEL
Date: 20251113

ACTIVE INGREDIENTS: BENZOCAINE 20 g/100 g
INACTIVE INGREDIENTS: POLYETHYLENE GLYCOL, UNSPECIFIED; SACCHARIN SODIUM; SORBIC ACID

5820342 TopCare Max Str Oral Pain Relief Gel

Drug Facts

Active ingredient

Benzocaine 20%

Purpose

Oral Pain Reliever

Use

- for the temporary relief of pain due to toothaches

Warnings

Methemoglobinemia warning: use of this product may cause methemoglobinemia, a serious condition that must be treated promptly because it reduces the amount of oxygen carried in blood. This can occur even if you have used this product before. Stop use and seek immediate medical attention if you or a child in your care develops:

- pale, gray or blue colored skin (cyanosis)
- headache
- rapid heart rate
- shortness of breath
- dizziness or lightheadedness
- fatigue or lack of energy

Allergy alert: do not use this product if you have a history of allergy to local anesthetics such as procaine, butacaine, benzocaine or other “caine” anesthetics

Do not use

- more than directed
- for more than 7 days unless told to do so by a dentist or doctor
- for teething
- in children under 2 years of age

Stop use and ask a doctor if

- swelling, rash, fever develops
- irritation, pain or redness persists or worsens
- symptoms do not improve in 7 days
- allergic reaction occurs

Keep out of reach of children. In case of overdose, get medical help or contact a Poison Control Center right away.

Directions

- cut open tip of tube on scoremark
- adults and children 2 years of age and older: apply a small amount of product to the cavity and around the the gum surrounding the teeth. Use up to 4 times daily or as directed by a dentist or doctor. Children under 12 years of age should be supervised in the use of this product.
- children under 2 years of age: do not use

Other information

- do not use if tip is cut prior to opening
- this preparation is intended for use in cases of toothache, only as a tempory expedient until a dentist can be consulted
- do not use continuously

INACTIVE INGREDIENT

Inactive ingredients flavor, polyethylene glycol, sodium saccharin, sorbic acid

DISTRIBUTED BY TOPCO ASSOCIATES LLC

ELK GROVE VILLAGE, IL 60057

QUESTIONS" 1-888-423-0139

topcare@topco.com www.topcarebrand.com